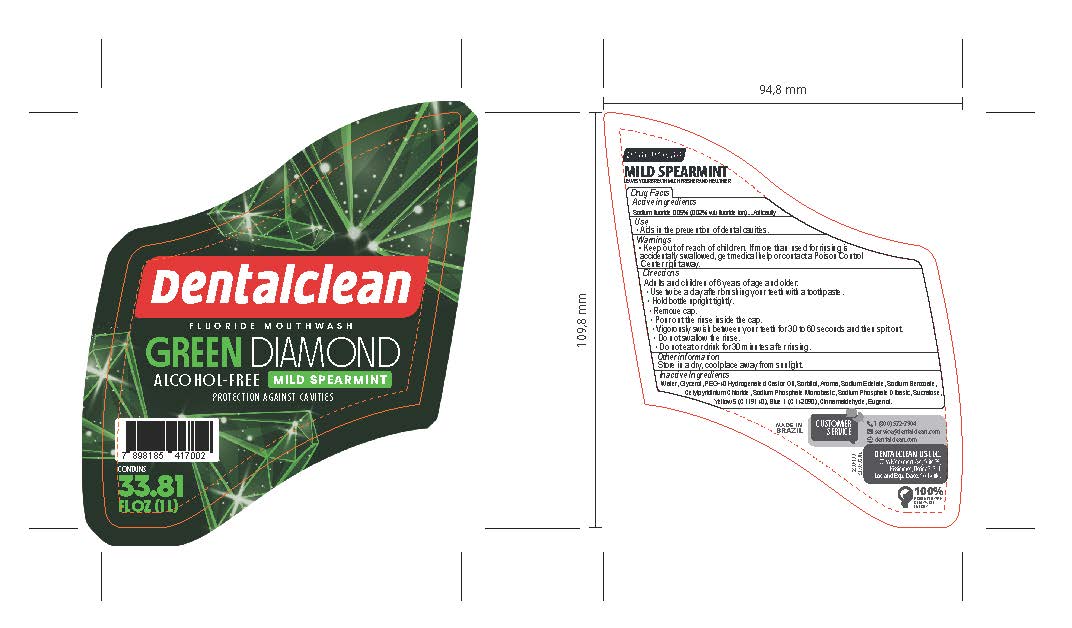 DRUG LABEL: Dentalclean Green Diamond Alcohol Free Mouthwash
NDC: 84035-012 | Form: RINSE
Manufacturer: Rabbit Indústria e Comércio de Produtos de Higiene Pessoal Ltda
Category: otc | Type: HUMAN OTC DRUG LABEL
Date: 20250714

ACTIVE INGREDIENTS: SODIUM FLUORIDE 0.2 mg/1 mL
INACTIVE INGREDIENTS: SUCRALOSE; CETYLPYRIDINIUM CHLORIDE ANHYDROUS; EDETATE DISODIUM; WATER; SODIUM PHOSPHATE, MONOBASIC, MONOHYDRATE; SORBITOL; FD&C BLUE NO. 1; SODIUM BENZOATE; EUGENOL; SODIUM PHOSPHATE DIBASIC DIHYDRATE; CINNAMALDEHYDE; YELLOW 5; PEG-40 HYDROGENATED CASTOR OIL; GLYCEROL FORMAL

Dentalclean Green Diamond Alcohol Free Mouthwash

ACTIVE INGREDIENT

Sodium fluoride 0.05%

PURPOSE

Anticavity

INDICATIONS AND USAGE

Useaids in the prevention of dental cavities

WARNINGS

WARNINGS: If more than used for brushing is accidentally swallowed, get medical help or contact poison control center right away.

Directions

Adults and children of 6 years of age and older:

• Use twice a day after brushing your teeth with a toothpaste.
•Remove cap
• Hold bottle upright and squeeze
•Pour out the rinse inside the cap
•Vigorously swish between your teeth for 30 to 60 seconds and then spit out
• Do not swallow the rinse.
• Do not eat or drink for 30 minutes after rinsing.

OTHER SAFETY INFORMATION

Store in a dry, cool place away from sunlight.

Inactive Ingredients

Water, Glycerol, PEG-40 Hydrogenated Castor Oil, Sorbitol, Aroma, Sodium Edetate, Sodium Benzoate, Cetylpyridinium Chloride, Sodium Phosphate Monobasic, Sodium Phosphate Dibasic, Sucralose, Yellow 5 (CI 19140), Blue 1 (CI 42090), Cinnamaldehyde, Eugenol.

Keep out of reach of children